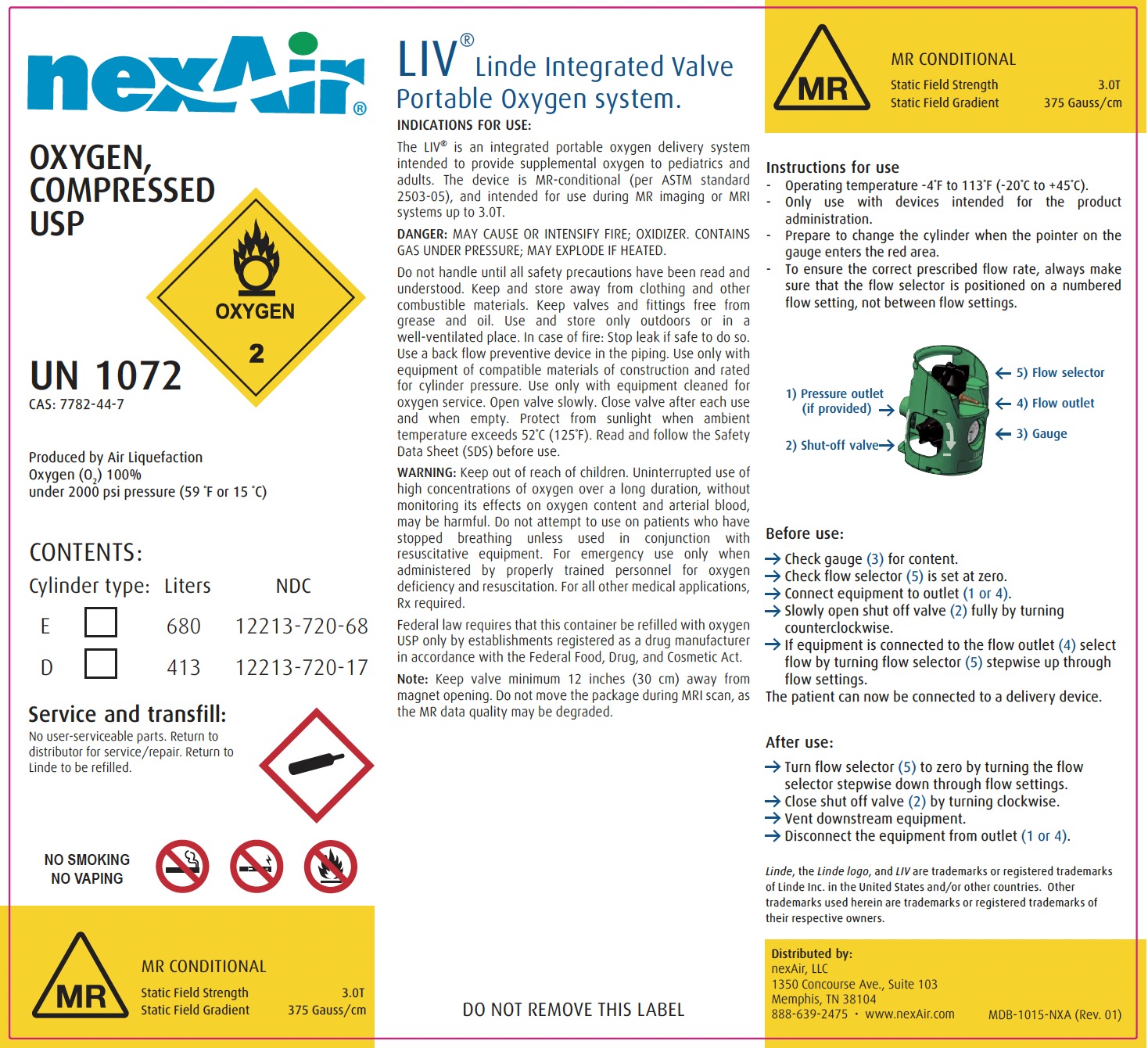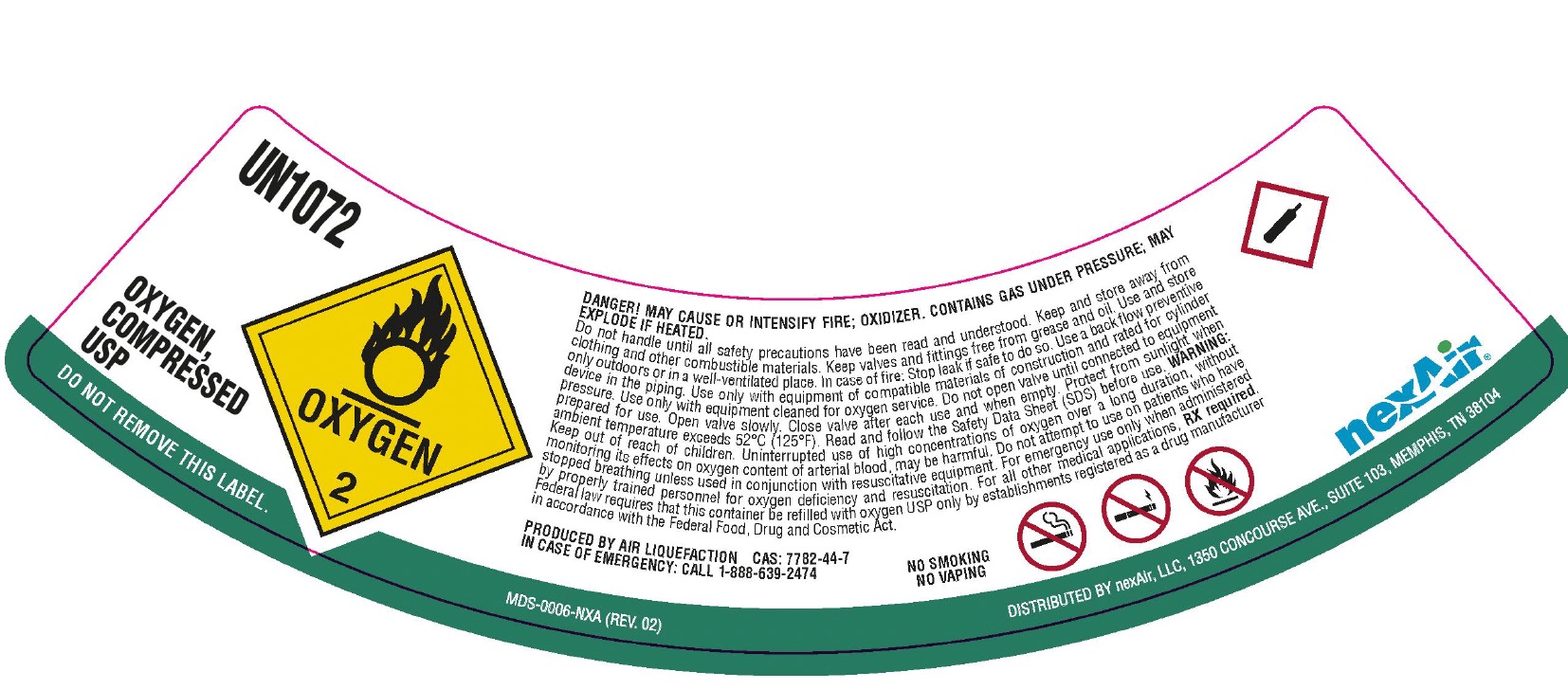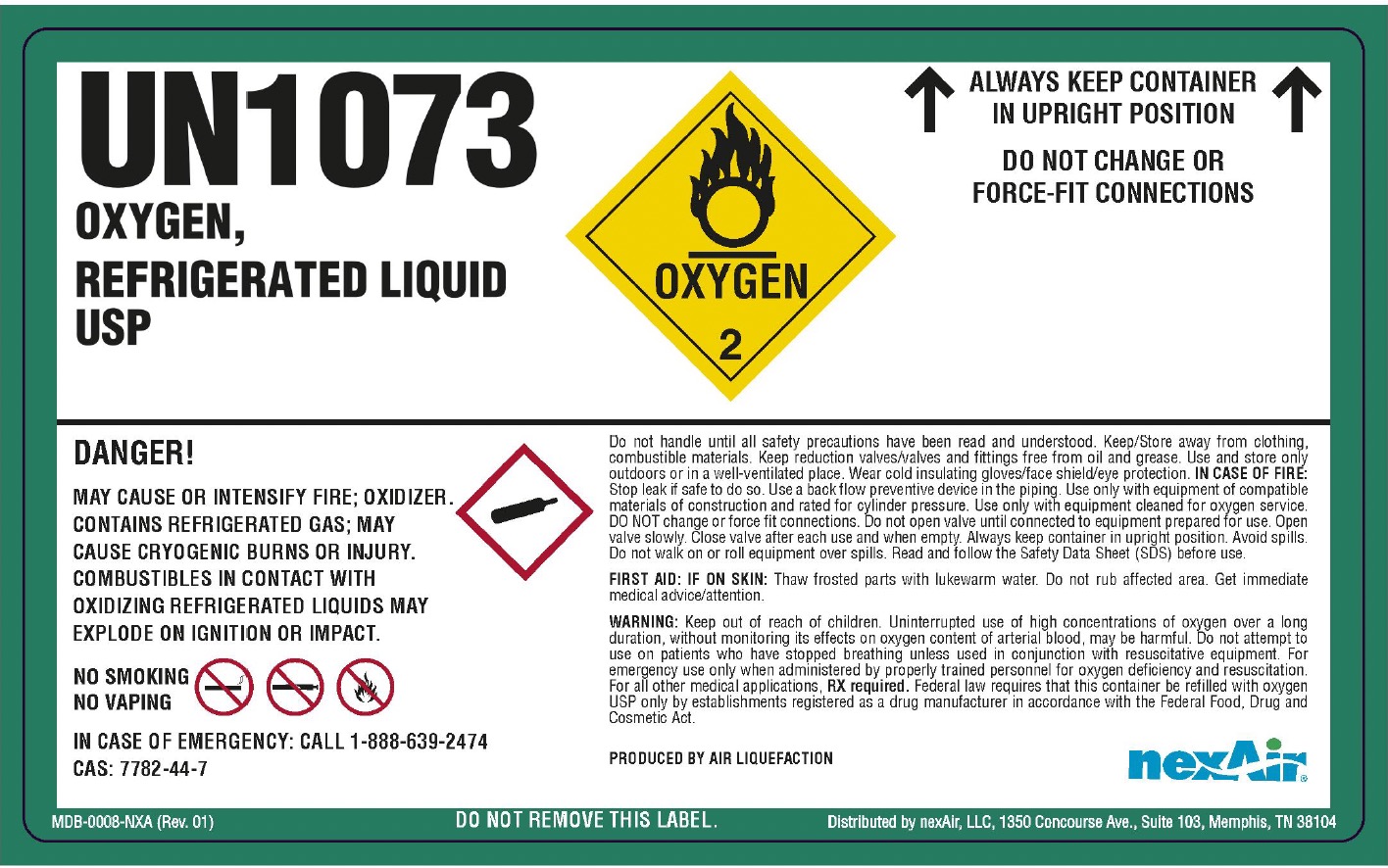 DRUG LABEL: Oxygen
NDC: 12213-720 | Form: GAS
Manufacturer: NexAir, LLC
Category: prescription | Type: HUMAN PRESCRIPTION DRUG LABEL
Date: 20251216

ACTIVE INGREDIENTS: OXYGEN 991 mL/1 L

Oxygen

PACKAGE LABEL

nexAir

OXYGEN, COMPRESSED USP

UN1072

CAS: 7782-44-7

Produced by Air Liquefaction

Oxygen (O2) 100% under 2000 psi pressure (59 F or 15 C)

CONTENTS:

Cylinder type: Liters NDC

E 680 12213-720-68

D 413 12213-720-17

Service and transfill: No user-serviceable parts. Return to distributor for service/repair. Return to Linde to be refilled.

NO SMOKING NO VAPING

MR CONDITIONAL

Static Field Strength 3.0T

Static Field Gradient 375 Gauss/cm

LIV Linde Integrated Valve Portable Oxygen system.

INDICATIONS FOR USE: The LIV is an integrated portable oxygen delivery system intented to provide supplemental oxygen to pediatrics and adults. The device is MR-conditional (per ASTM Standard 2503-05), and intended for use during MR imaging or MRI systems up to 3.0T.

DANGER: MAY CAUSE OR INTENSIFY FIRE; OXIDIZER. CONTAINS GAS UNDER PRESURE; MAY EXPLODE IF HEATED.

Do not handle until all safety precautions have been read and understood. Keep and store away from clothing and other combustible materials. Keep valves and fittings free from grease and oil. Use and store only outdoors or in a well-ventilated place. In case of fire: Stop leak if safe to do so. Use a back flow preventive device in the piping. Use only with equipment of compatible materials of construction and rated for cylinder pressure. Use only with equipment cleaned for oxygen service. Open valve slowly. Close valve after each use and when empty. Protect form sunlight when ambient temperature exceeds 52 C (125 F). Read and follow the Safety Data Sheet (SDS) before use.

WARNING: Keep out of reach of children. Uninterrupted use of high concentrations of oxygen over a long duration, without monitoring its effect on oxygen content and arterial blood, may be harmful. Do not attempt to use on patients who have stopped breathing unless used in conjunction with resuscitative equipment. For emergency use only when administered by properly trained personnel for oxygen deficiency and resuscitation. For all other medical applications, Rx required.

Federal law requires that this container be refilled with oxygen USP only by establishments registered as a drug manufacturer in accordance with the Federal Food, Drug, and Cosmetic Act.

Note: Keep valve minimum 12 inches (30 cm) away from magnet opening. Do not move the package during MRI scan, as the MR data quality may be degraded.

DO NOT REMOVE THIS LABEL

MR CONDITIONAL

Static Field Strength 3.0T

Static Field Gradient 375 Gauss/cm

Instructions for use

Operating temperature -4 F to 113 F (-20 C to +45 C).

Only use with devices intended for the product administration.

Prepare to change the cylinder when the pointer on the gauge enters the red area.

To ensure the correct prescribed flow rate, always make sure that the flow selector is positioned on a numbered flow setting, not between the flow settings.

1) Pressure outlet (if provided) 5) Flow Selector

2) Shut-off valve 4) Flow outlet

3) Gauge

Before use:

Check gauge (3) for content.

Check flow selector (5) is set at zero.

Connect equipment to outlet (1 or 4).

Slowly open shut off valve (2) fully by turning counterclockwise.

If equipment is connected to the flow outlet (4) select flow by turning flow selector (5) stepwise up through flow settings.

The patient can now be connected to a delivery device

After use:

Turn flow selector (5) to zero by turning the flow selector stepwise down through flow settings.

Close shut off valve (2) by turning clockwise.

Vent downstream equipment.

Disconnect the equipment from outlet (1 or 4).

Distributed by:

nexAir, LLC

1350 Concourse Ave., Suite 103

Memphis, TN 38104

888-639-2475 www.nexAir.com

PACKAGE LABEL

UN1072

OXYGEN, COMPRESSED USP

DO NOT REMOVE THIS LABEL.

DANGER! MAY CAUSE OR INTENSIFY FIRE; OXIDIZER. CONTAINS GAS UNDER PRESSURE; MAY EXPLODE IF HEATED.

Do not handle until all safety precautions have been read and understood. Keep and store away from clothing and other combustible materials. Keep valves and fittings free from grease and oil. Use and store only outdoors or in a well-ventilated place. In case of fire: Stop leak if safe to do so. Use a back flow preventive device in the piping. Use only with equipment of compatible materials of construction and rated for cylinder pressure. Use only with equipment cleaned for oxygen service. Do not open valves until connected to equipment prepared for use. Open valve slowly. Close valve after each use and when empty. Protect from sunlight when ambient temperature exceeds 52 C (125 F). Read and follow the Safety Data Sheet (SDS) before use. WARNING: Keep out of reach of children. Uninterrupted use of high concentrations of oxygen over a long duration, without monitoring its effect on oxygen content of arterial blood, may be harmful. Do not attempt to use on patients who have stopped breathing unless used in conjunction with resuscitative equipment. For emergency use only when administered by properly trained personnel for oxygen deficiency and resuscitation. For all other medical applications, RX required. Federal law requires that this container be refilled with oxygen USP only by establishments registered as a drug manufacturer in accordance with the Federal Food, Drug and Cosmetic Act.

PRODUCED BY AIR LIQUFACTION CAS: 7782-44-7

IN CASE OF EMERGENCY: CALL 1-888-639-2474

NO SMOKING

NO VAPING

nexAir

Distributed by nexAir, LLC, 1350 Concourse Ave., Suite 103, Memphis, TN 38104

PACKAGE LABEL

UN1073

OXYGEN, REFRIGERATED LIQUID USP

ALWAYS KEEP CONTAINER IN UPRIGHT POSITION

DO NOT CHANGE OR FORCE-FIT CONNECTIONS

DANGER!

MAY CAUSE OR INTENSIFY FIRE; OXIDIZER. CONTAINS REFRGIERATED GAS; MAY CAUSE CRYOGENIC BURNS OR INJURY. COMBUSTIBLES IN CONTACT WITH OXIDIZING REFRIGERATED LIQUIDS MAY EXPLODE ON IGNITION OR IMPACT.

NO SMOKING

NO VAPING

IN CASE OF EMERGENCY: CALL 1-88-639-2474

CAS: 7782-44-7

DO NOT REMOVE THIS LABEL.

Do not handle until all safety precautions have been read and understood. Keep/Store away from combustible materials, clothing. Keep reduction valves/valves and fittings free from oil and grease. Use and store only outdoors or in a well-ventilated place. Wear cold insulating gloves/face shield/eye protection. IN CASE OF FIRE: Stop leak if safe to do so. Use a back flow preventive device in the piping. Use only with equipment of compatible materials of construction and rated for cylinder pressure. Use only with equipment cleaned for oxygen service. Do NOT change or force fit connections. Do not open valve until connected to equipment prepared for use. Open valve slowly. Close valve after each use and when empty. Always keep container in upright position. Avoid spills. Do not walk on or roll equipment over spills. Read and follow the Safety Data Sheet (SDS) before use.

FIRST AID: IF ON SKIN: Thaw frosted parts with lukewarm water. Do not rub affected area. Get immediate medical advice/attention.

WARNING: Keep out of reach of children. Uninterrupted use of high concentrations of oxygen over a long duration, without monitoring its effects on oxygen content of arterial blood, may be harmful. Do not attempt to use on patients who have stopped breathing unless used in conjunction with resuscitative equipment. For emergency use only when administered by properly trained personnel for oxygen deficiency and resuscitation. For all other medical applications, RX required. Federal law requires that this container be refilled with oxygen USP only by establishments registered as a drug manufacturer in accordance with the Federal Food, Drug and Cosmetic Act.

PRODUCED BY AIR LIQUEFACITON

nexAir

Distributed by nexAir, LLC, 1350 Concourse Ave., Suite 103, Memphis, TN 38104